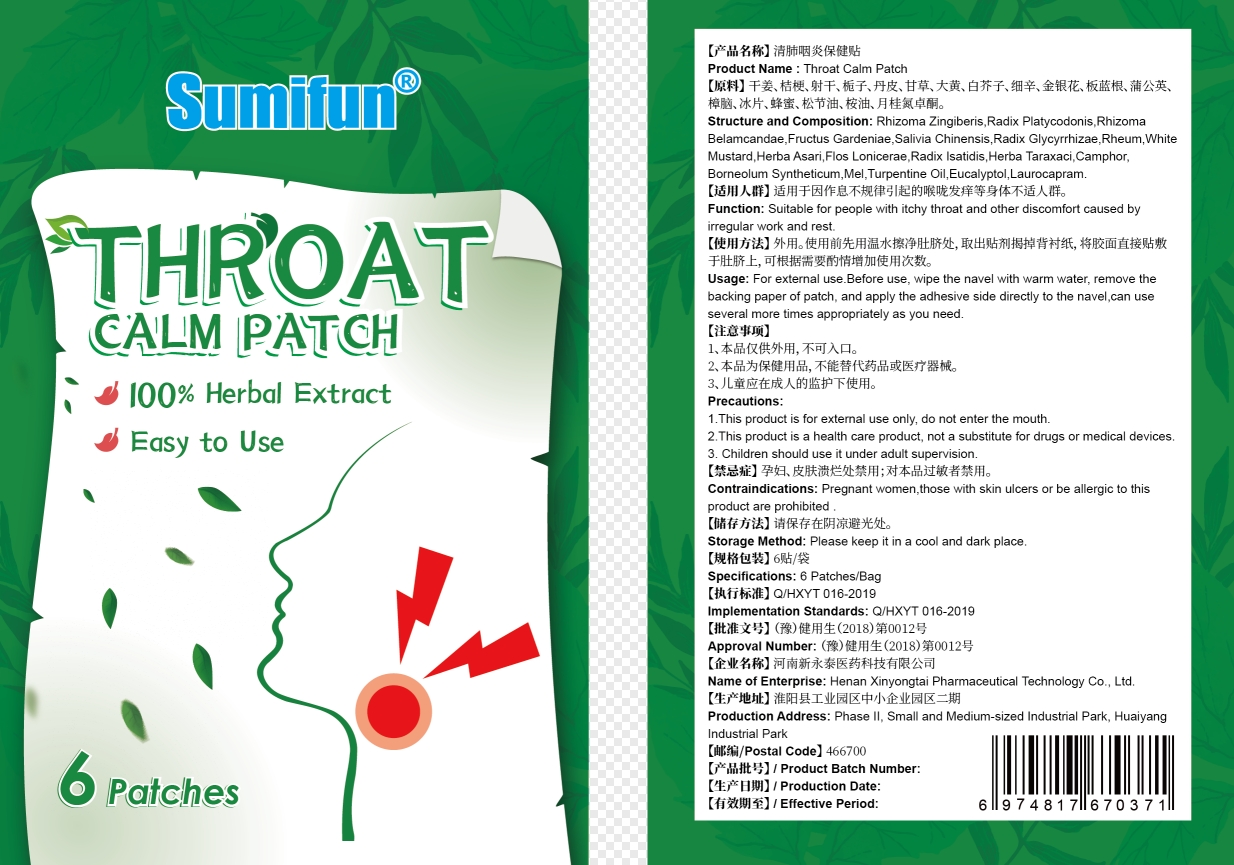 DRUG LABEL: Throat Calm Patch
NDC: 83675-011 | Form: PATCH
Manufacturer: Guangzhou Hanhai Trading Co., Ltd
Category: otc | Type: HUMAN OTC DRUG LABEL
Date: 20230920

ACTIVE INGREDIENTS: GINGER 14 g/100 1
INACTIVE INGREDIENTS: IRIS DOMESTICA ROOT; RHEUM ACUMINATUM ROOT; ASARUM HETEROTROPOIDES; TURPENTINE OIL; EUCALYPTOL; GARDENIA JASMINOIDES FRUIT; HONEY; LAUROCAPRAM; BORNEOL; WHITE MUSTARD SEED; CAMPHOR (NATURAL); PLATYCODON GRANDIFLORUM ROOT; LICORICE; TARAXACUM OFFICINALE FLOWERING TOP; LIMONENE, (+/-)-

Active Ingredient

Rhizoma Zingiberis 14.0%

Purpose

Relieve itchy

Use

Throat Calm Patch to help relieve itchy

Warnings

For external use only. Do not take it internally.

Keep Out Of Reach Of Children
Prohibited for those with damaged skin.

Do not use

Product shall not be eat

When Using

Do not stick around eyes and mouth,This product cannot replace drugs.

Stop Use

In case of adverse reactions, please stop using this product.If the symptoms.

Ask Doctor

ask doctor in case of adverse reactions

Keep Oot Of Reach Of Children

Keep Out Of Reach Of Children

Directions

Take one piece of this product when needed, remove the waxpaper,

stick to the desired area and press the surrounding, replace it every 8-12 hours.

Children should be used under adult supervision.

Other information

Store the product in a cool, dry and well-ventilated place

Avoid direct sunlight

Inactive ingredients

Radix Platycodonis,

RhizomaBelamcandae.

Fructus Gardeniae.

Salivia Chinensis.

Radix Glycyrrhizae.

Rheum.

White Mustard,

Herba Asari,

Flos Lonicerae Radix lsatidis,

Herba Taraxaci,

Camphor,
Borneolum Syntheticum,

Mel.

Turpentine Oil,

Eucalyptol,

Laurocapram.